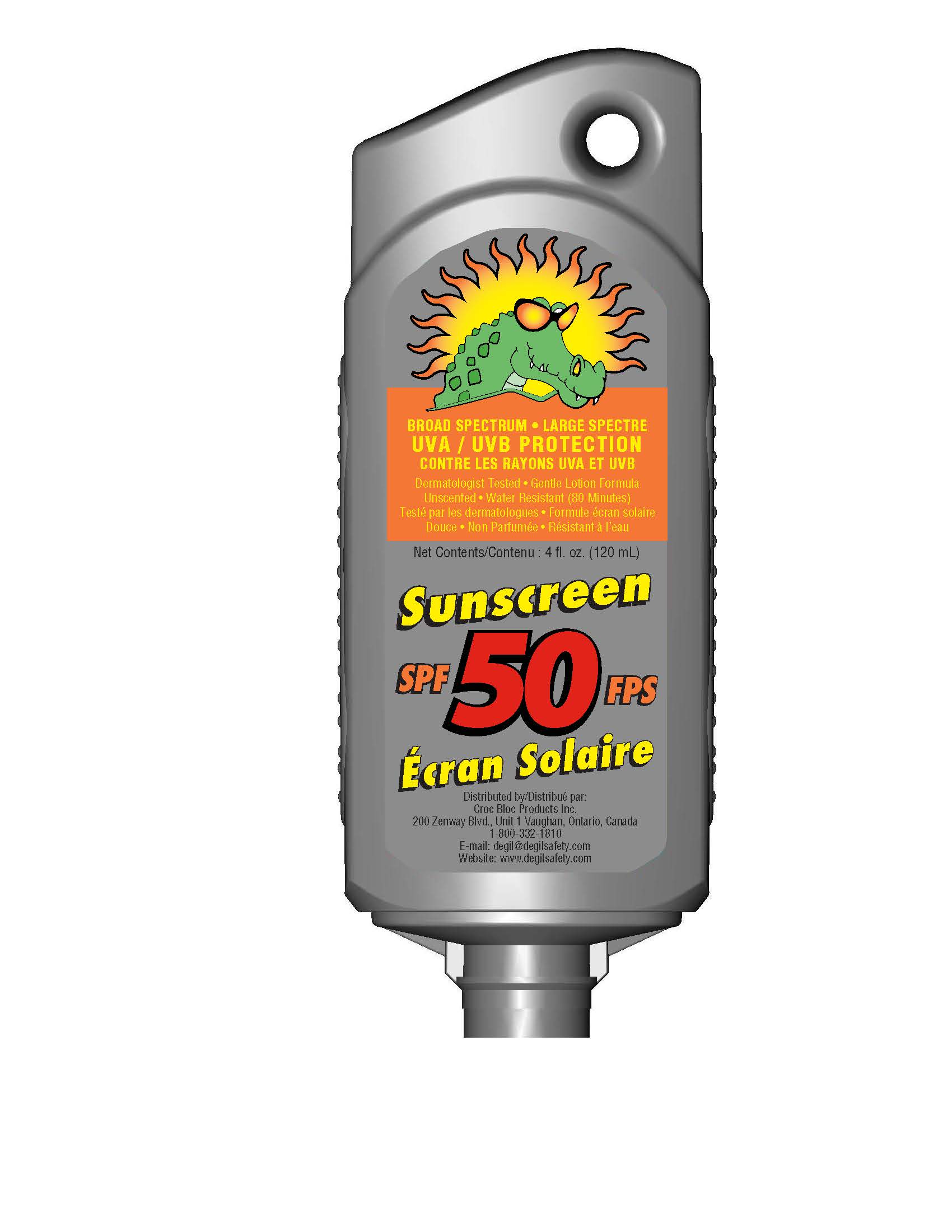 DRUG LABEL: CROC BLOC BROAD SPECTRUM SPF 50 FPS ECRAN SOLAIRE
NDC: 58331-050 | Form: LOTION
Manufacturer: Degil Safety Products (1989) Inc.
Category: otc | Type: HUMAN OTC DRUG LABEL
Date: 20221121

ACTIVE INGREDIENTS: OXYBENZONE 4 g/100 mL; OCTISALATE 5 g/100 mL; HOMOSALATE 13 g/100 mL; OCTOCRYLENE 7 g/100 mL; AVOBENZONE 3 g/100 mL
INACTIVE INGREDIENTS: BENZYL ALCOHOL; DIMETHICONE; TOCOPHEROL; METHYLPARABEN; PROPYLPARABEN; POLYGLYCERYL-3 DISTEARATE; EDETATE DISODIUM; TROLAMINE; SORBITOL; ALUMINUM STARCH OCTENYLSUCCINATE; SORBITAN ISOSTEARATE; VINYLPYRROLIDONE/EICOSENE COPOLYMER; WATER; STEARIC ACID; CARBOXYPOLYMETHYLENE

Active Ingredients

Homosalate 13.0% w/w

Octocylene 7.0% w/w

Octisalate 5.0% w/w

Oxybenzone 4.0% w/w

Avobenzome 3.0% w/w

Purpose

- Sunscreen

Uses

- Helps prevent sunburn

Warnings

For external use only

Do not use on damaged or broken skin

Keep out of reach of children

- May stain or damage some fabrics or surfaces

When using this product

- Avoid contact with eyes. Rinse with water to remove.

Stop use and ask doctor if

- Rash or irritation develops and lasts

Directions

- Apply liberally and evenly to dry skin 15 minutes before exposure to the sun. Reapply every 2 hours to insure adequate UV protection or 80 minutes after swimming, perspiring heavily, or immediately after washing and towel drying.
- For children under 6 months of age: Ask a doctor

Other Information

- Protect the product from excessive heat and direct sun

Inactive Ingredients

Aqua, Sorbitol, Aluminum Starch Octenylsuccinate VP/Eicosene Copolymer, Stearic Acid, Triethanolamine, Sorbitan Isostearate, Benzyl Alcohol, Dimethicone, Tocopherol, Polyglyceryl-3 Distearate, Methylparaben, Carbomer, Propylparaben, Disodium EDTA.

PACKAGE LABEL

UVA / UVB PROTECTION

CONTRE LES RAYONS UVA ET UVB

Dermatologist Tested • Gentle Lotion formula

Unscented • Water Resistant (80 Minutes)

Testé par les dermatologues • Formule écran solaire

Douce • Non Parfumée • Résistant à I'eau

Sunscreen

SPF 50 FPS

Écran Solaire

Distributed by/Distribué par:

Croc Bloc Products Inc.

200 Zenway Blvd., Unit 1 Vaughan, Ontario, Canada

1-800-332-1810

Email: degil@degilsafety.com

Website: www.degilsafety.com